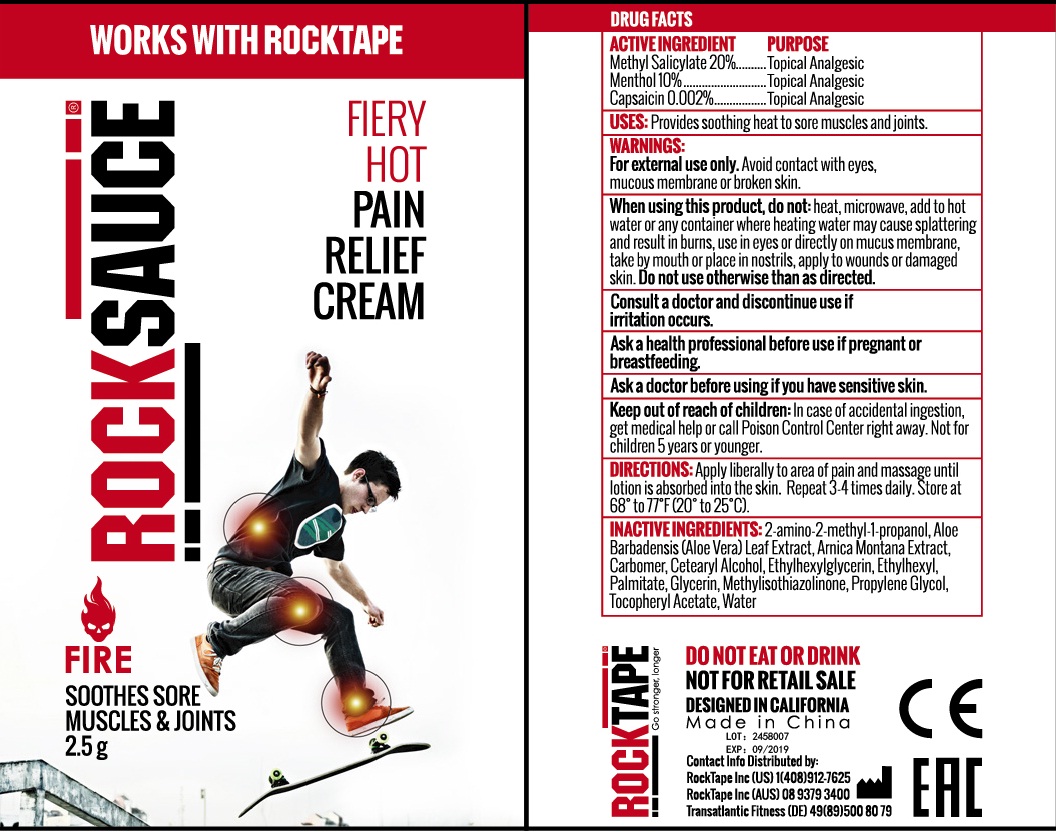 DRUG LABEL: rocksauce fire
NDC: 73344-104 | Form: CREAM
Manufacturer: NINGBO SANTE YING MEDICALAND HEALTHDEVELOPMENT CO.,LTD
Category: otc | Type: HUMAN OTC DRUG LABEL
Date: 20190929

ACTIVE INGREDIENTS: METHYL SALICYLATE 0.02 g/0.1 g; MENTHOL 0.01 g/0.1 g; CAPSAICIN 0.000002 g/0.1 g
INACTIVE INGREDIENTS: CARBOMER 940; ISOPROPYL ALCOHOL; ISOPROPYL MYRISTATE; SILICON DIOXIDE; GLYCERIN; ETHYLHEXYLGLYCERIN; PROPYLENE GLYCOL; METHYLISOTHIAZOLINONE; WATER

rocksauce FIRE

Active ingredients

Methyl Salicylate 20%

Menthol USP 10%

Capsaicin 0.002%

Purpose

Topical Analgesic

Uses:

For temporary relief minor muscular discomfort

Warnings:

For external use only.

Avoid contact with eyes, mucous membrane or broken skin

Keep out of reach of children.

if accidentally ingested, getmedical help or contact a Poison Control Center immediately.

Directions:

For the temporary relief of minor muscular discomfort. See important warnings under "When using this product". Not for use on children 5 years or younger. Apply liberally to painful area and massage until lotion is absorbed into the skin. Repeat 3-4 times daily. Store at 68 to 77F (20 to 25 C)

When using this product

do not heat, microwave, and to hot water or any container where heating water may cause splattering and result in burns, use in eyes or directly on mucus membrans, take by mouth or place in nostrill, apply to wounds or damaged skin. Do not use otherwise than as directed

Consult a doctor and discontinus use.

if conditions persist for more than 1 week or reocur.

Inactive ingredients:

2-amino-2-methyl-1-propanol, Aloe barbadensis (aloe vera) Leaf Extract, Arnica Montana Extract, Carbomer, Cetearyl Alcohol, Ethylhexylglycerin, Ethylhexyl, Palmitate, Glycerin, Methylisothiazolinone, Propylene Glycol, Tocopheryl Acetate, Water